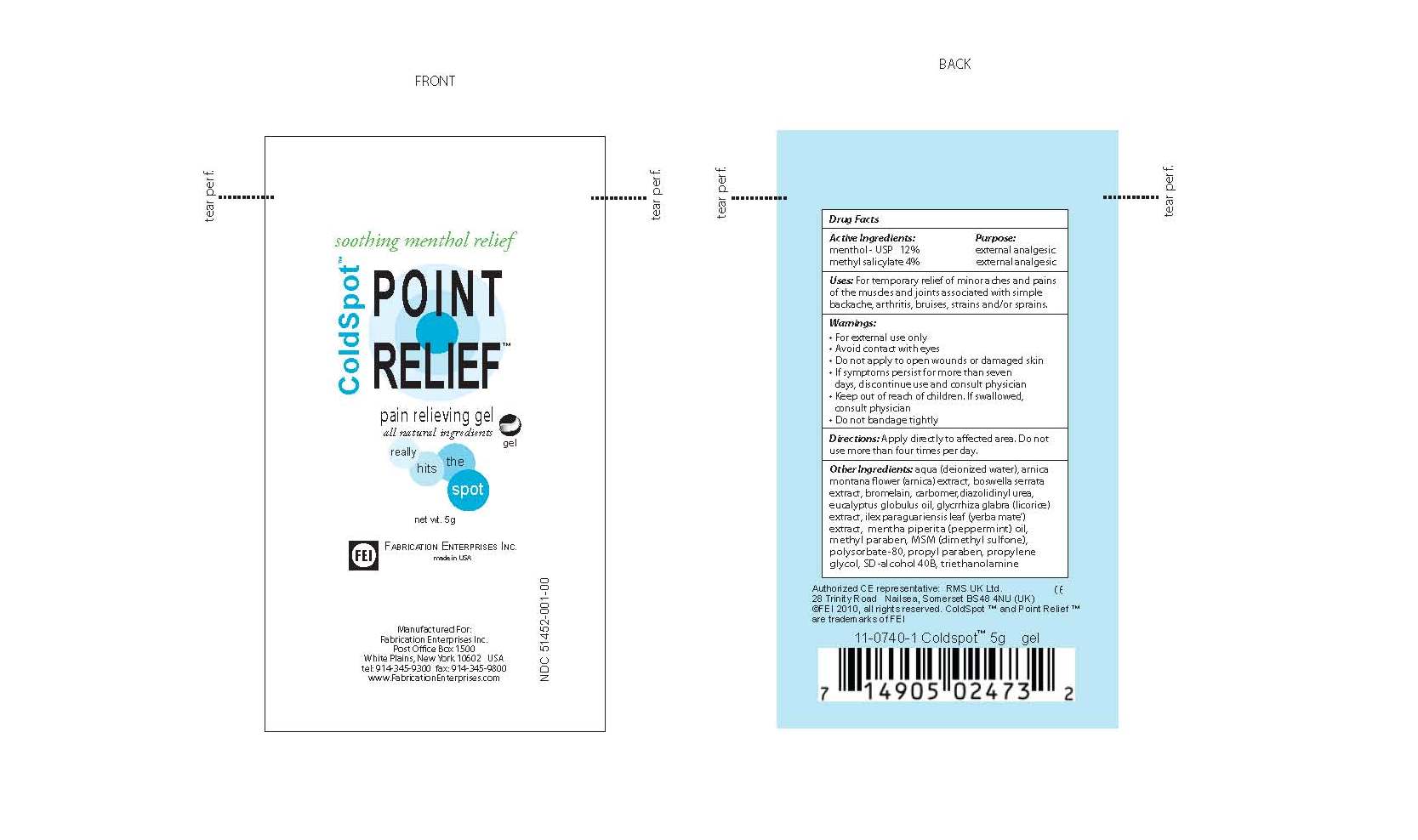 DRUG LABEL: Cold Spot
NDC: 51452-001 | Form: GEL
Manufacturer: Fabrication Enterprises
Category: otc | Type: HUMAN OTC DRUG LABEL
Date: 20101005

ACTIVE INGREDIENTS: Menthol 0.6 g/5 g; METHYL SALICYLATE 0.2 g/5 g
INACTIVE INGREDIENTS: water; ARNICA CORDIFOLIA FLOWER; CHONDROITIN SULFATE (BOVINE); Citric Acid; EUCALYPTUS GLOBULUS LEAF; Glucosamine sulfate; Ilex Paraguariensis Leaf; Isopropyl Alcohol; Peppermint Oil; Dimethyl Sulfone; polysorbate 20; alcohol

Cold Spot Point Relief Pain relieving Gel - 5 G

Active Ingredients: Menthol, methyl salicylate

INACTIVE INGREDIENT

Inactive Ingredients: deionized water, arnica, chondroitin sulfate, citirc acid, euclayptus oil, glucosamine sulfate, ilex paraguariesis leaf, isopropyl alcohol, peppermint oil, dimethyl sulfone, polysorbate-20, SD alcohol 40B.

Keep out of reach of children. If swallowed consult physician

WARNINGS

Warnings Section: For external use only, avoid contact with eyes, do not apply to open wounds or damaged skin, if symptoms persist for more than seven days discontinue use and consult physician, keep out of reach of children and if swallowed consult physician, do not bandage tightly.

PURPOSE

pain relieving gel

INDICATIONS AND USAGE

Use: For temporary relief of minor aches and pains of the muscles and joints associated with simple backache, arthritis, bruises, strains and/or sprains.

DOSAGE AND ADMINISTRATION

Apply directly to effected area. Do not use more than four times per day.

PACKAGE LABEL

ColdSpot Point Relief Pain Relieving spray, all natural ingredients.